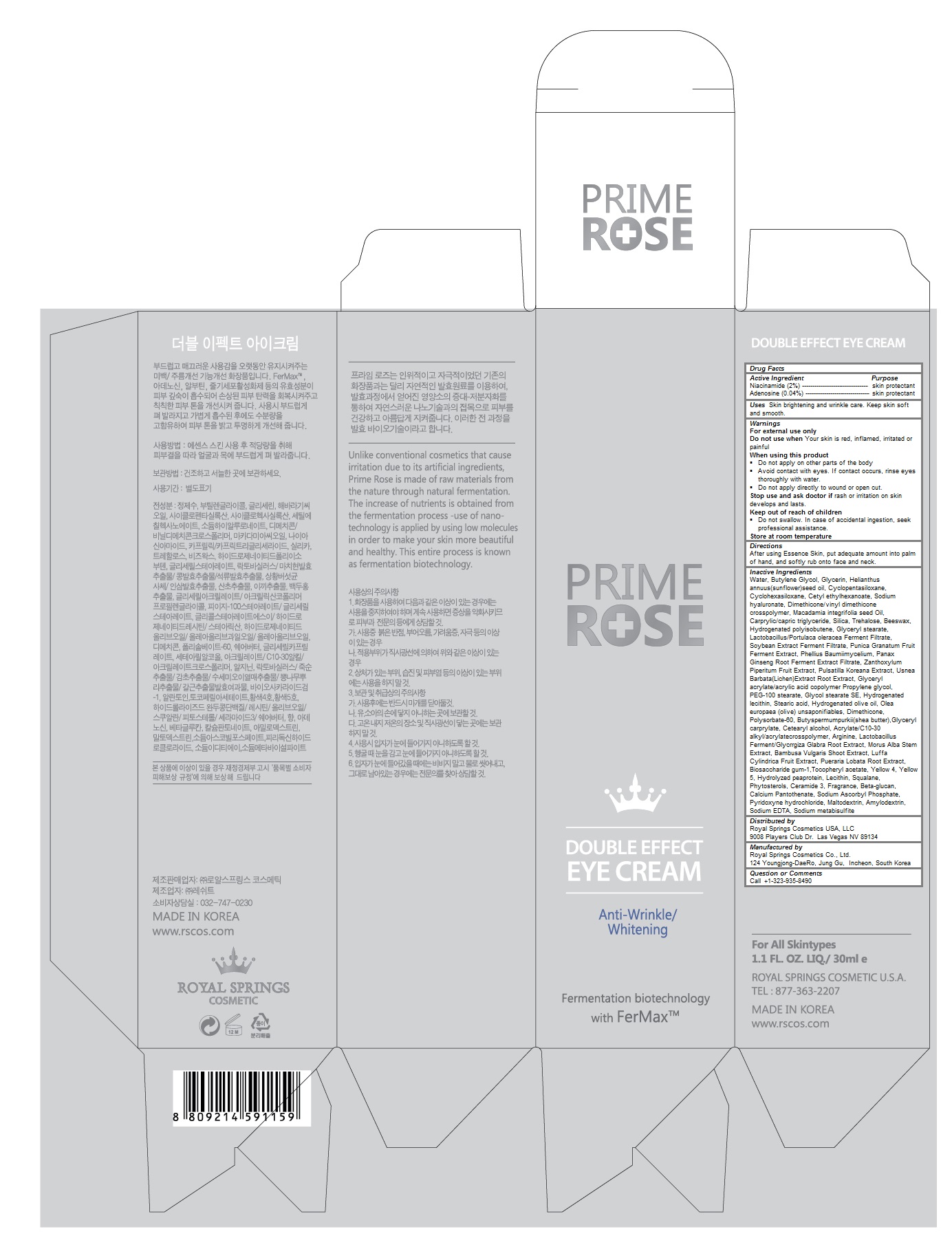 DRUG LABEL: PRIMEROSE DOUBLE EFFECT EYE
NDC: 69888-105 | Form: CREAM
Manufacturer: Royal Springs Cosmetics USA, LLC
Category: otc | Type: HUMAN OTC DRUG LABEL
Date: 20190115

ACTIVE INGREDIENTS: NIACINAMIDE 0.02 1/30 mL; ADENOSINE 0.0004 1/30 mL
INACTIVE INGREDIENTS: WATER; BUTYLENE GLYCOL; GLYCERIN; SUNFLOWER OIL; CYCLOMETHICONE 5; CYCLOMETHICONE 6; CETYL ETHYLHEXANOATE; HYALURONATE SODIUM; DIMETHICONE/VINYL DIMETHICONE CROSSPOLYMER (HARD PARTICLE); MACADAMIA OIL; MEDIUM-CHAIN TRIGLYCERIDES; SILICON DIOXIDE; TREHALOSE; YELLOW WAX; HYDROGENATED POLYBUTENE (1300 MW); GLYCERYL MONOSTEARATE; ASIAN GINSENG; ZANTHOXYLUM PIPERITUM FRUIT PULP; PULSATILLA KOREANA ROOT; PEG-100 STEARATE; GLYCOL STEARATE; HYDROGENATED SOYBEAN LECITHIN; STEARIC ACID; HYDROGENATED OLIVE OIL; OLEA EUROPAEA (OLIVE) OIL UNSAPONIFIABLES; DIMETHICONE; POLYSORBATE 60; SHEA BUTTER; GLYCERYL CAPRYLATE; CETOSTEARYL ALCOHOL; CARBOMER INTERPOLYMER TYPE A (ALLYL SUCROSE CROSSLINKED); ARGININE; MORUS ALBA STEM; BAMBUSA VULGARIS STEM; LUFFA AEGYPTIACA FRUIT; PUERARIA MONTANA VAR. LOBATA ROOT; BIOSACCHARIDE GUM-1; .ALPHA.-TOCOPHEROL ACETATE; FD&C YELLOW NO. 5; EGG PHOSPHOLIPIDS; SQUALANE; .BETA.-SITOSTEROL; CERAMIDE NP; CALCIUM PANTOTHENATE; SODIUM ASCORBYL PHOSPHATE; PYRIDOXINE HYDROCHLORIDE; MALTODEXTRIN; EDETATE SODIUM; SODIUM METABISULFITE

PRIMEROSE DOUBLE EFFECT EYE CREAM